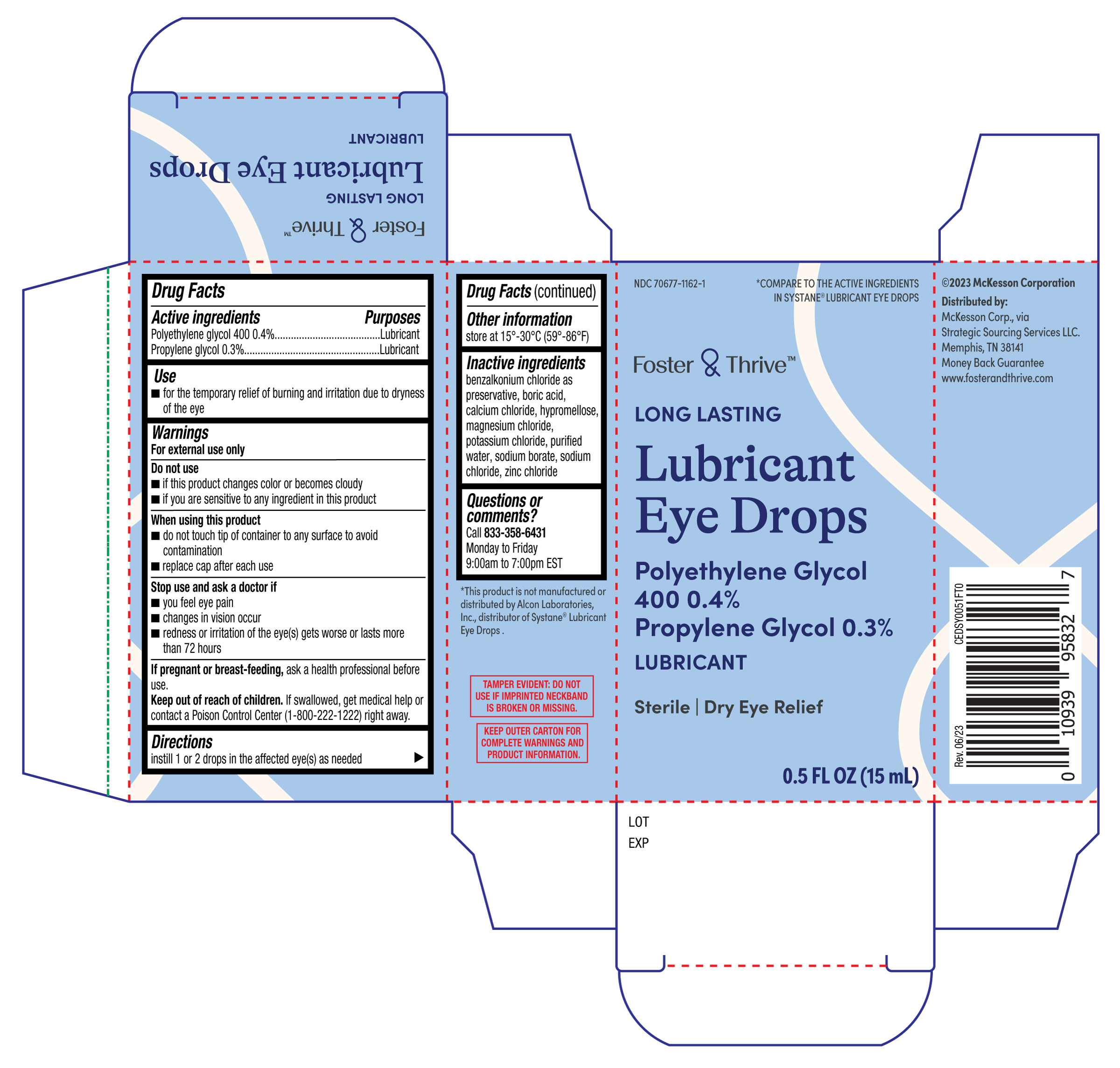 DRUG LABEL: Foster and Thrive Long Lasting Lubricant Eye Drops
NDC: 70677-1162 | Form: SOLUTION/ DROPS
Manufacturer: Strategic Sourcing Services LLC
Category: otc | Type: HUMAN OTC DRUG LABEL
Date: 20251230

ACTIVE INGREDIENTS: PROPYLENE GLYCOL 0.3 g/100 mL; POLYETHYLENE GLYCOL 400 0.4 g/100 mL
INACTIVE INGREDIENTS: WATER; SODIUM CHLORIDE; POTASSIUM CHLORIDE; CALCIUM CHLORIDE; HYPROMELLOSE, UNSPECIFIED; BORIC ACID; SODIUM BORATE; BENZALKONIUM CHLORIDE; MAGNESIUM CHLORIDE; ZINC CHLORIDE

Foster and Thrive Long Lasting Lubricant Eye Drops 15mL (PLD)

Active Ingredients

Polyethylene glycol 400 0.4%

Propylene glycol 0.3%

Purposes

Lubricant

Lubricant

Use

- for the temporary relief of burning and irritation due to dryness if the eye

Warnings

For external use only

Do not use

- if this product changes color or becomes cloudy
- if you are sensitive to any ingredient in this product

When using this product

- do not touch tip of container to any surface to avoid contamination
- replace cap after each use

Stop use and ask a doctor if

- you feel eye pain
- changes in vision occur
- redness or irritation of the eye(s) gets worse or lasts more than 72 hours

If pregnant or breast-feeding,

ask a health professional before use.

Keep out of reach of children.

If swallowed, get medical help or contact a Poison Control Center (1-800-222-1222) right away.

Directions

instill 1 or 2 drops in the affected eye(s) as needed

Other information

store at 15°-30°C (59°-86°F)

Inactive ingredients

benzalkonium chloride as preservative, boric acid, calcium chloride, hypromellose, magnesium chloride, potassium chloride, purified water, sodium borate, sodium chloride, zinc chloride

Questions or comments?

Call 833-358-6431

Monday to Friday

9:00am to 7:00pm EST